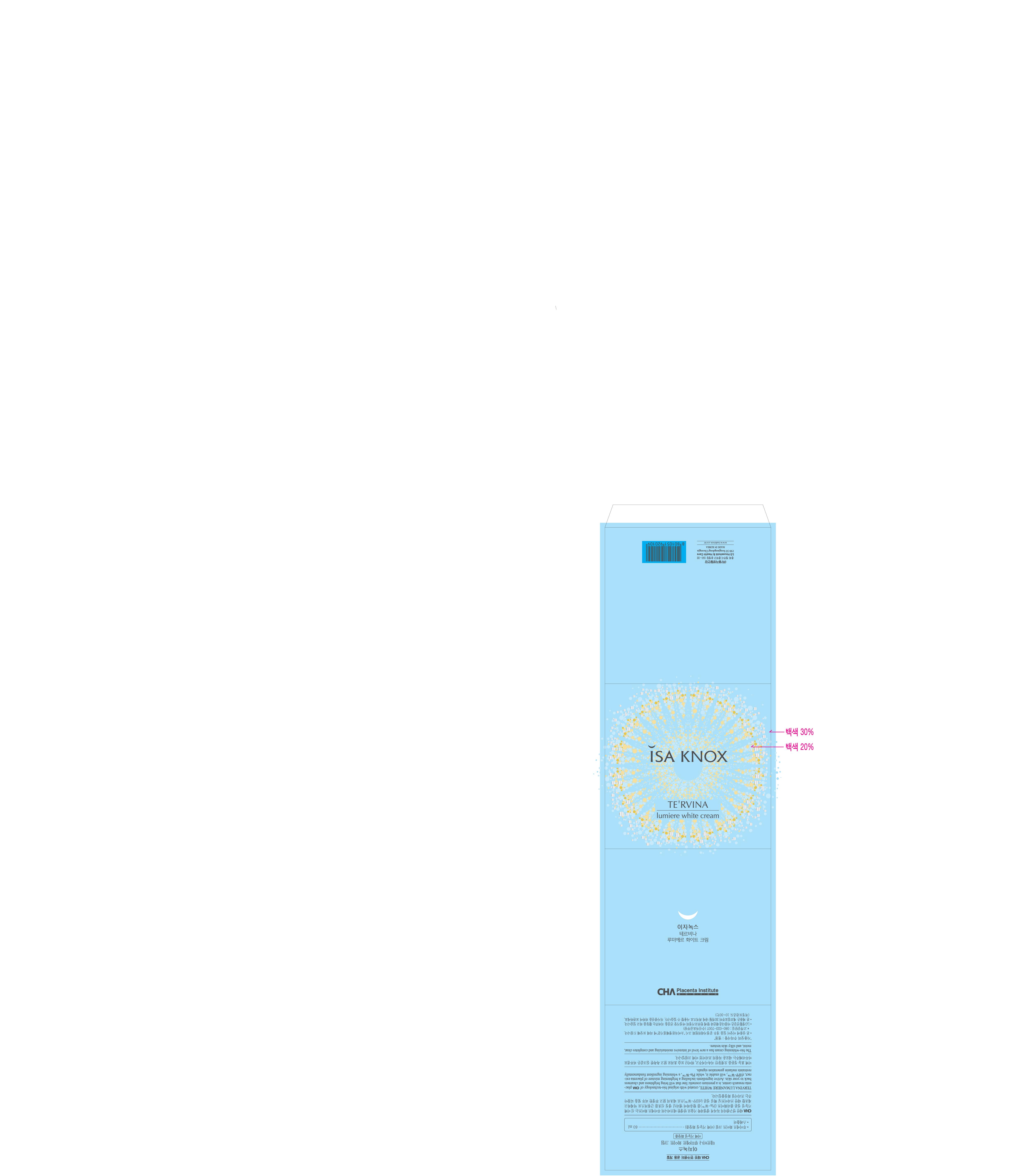 DRUG LABEL: ISAKNOX TERVINA LUMIERE WHITE
NDC: 53208-530 | Form: CREAM
Manufacturer: LG Household and Healthcare, Inc.
Category: otc | Type: HUMAN OTC DRUG LABEL
Date: 20120515

ACTIVE INGREDIENTS: METHYL UNDECENOYL LEUCINATE 0.1 mL/100 mL
INACTIVE INGREDIENTS: WATER; BUTYLENE GLYCOL; CYCLOMETHICONE 5; GLYCERIN; BIOSACCHARIDE GUM-1; MEDIUM-CHAIN TRIGLYCERIDES; NEOPENTYL GLYCOL DICAPRATE; TREHALOSE; DIMETHICONE; PHENOXYETHANOL; METHYLPARABEN; ETHYLPARABEN; BUTYLPARABEN; PROPYLPARABEN; ISOBUTYLPARABEN; C14-22 ALCOHOLS; C12-20 ALKYL GLUCOSIDE; GLYCERYL MONOSTEARATE; PEG-100 STEARATE; SQUALANE; CETEARYL OLIVATE; SORBITAN OLIVATE; HYALURONATE SODIUM; 1,2-HEXANEDIOL; TROMETHAMINE; EDETATE TRISODIUM

Drug Fact

ACTIVE INGREDIENT

METHYL UNDECENOYL LEUCINATE 0.1%

PURPOSE

Whitening cream

Stop use if rash or irritation develops and lasts.

WHEN USING

Keep out of eyes. Rinse with water to remove

INDICATIONS AND USAGE

Use to whiten skin.

Keep out of reach of children. Is swallowed, get medical help or contact a Poison Control Center right away.

INACTIVE INGREDIENT

WATER
BUTYLENE GLYCOL
CYCLOMETHICONE 5
GLYCERIN
BIOSACCHARIDE GUM-1
MEDIUM-CHAIN TRIGLYCERIDES
NEOPENTYL GLYCOL DICAPRATE
TREHALOSE
DIMETHICONE
PHENOXYETHANOL
METHYLPARABEN
ETHYLPARABEN
BUTYLPARABEN
PROPYLPARABEN
ISOBUTYLPARABEN
C14-22 ALCOHOLS
C12-20 ALKYL GLUCOSIDE
GLYCERYL MONOSTEARATE
PEG-100 STEARATE
SQUALANE
CETEARYL OLIVATE
SORBITAN OLIVATE
HYALURONATE SODIUM
1,2-HEXANEDIOL
TROMETHAMINE
EDETATE TRISODIUM

DOSAGE AND ADMINISTRATION

Apply after the Eyecream